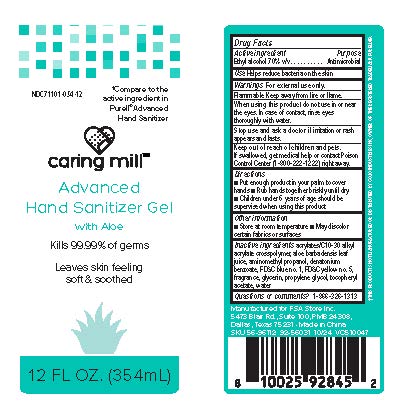 DRUG LABEL: Caring Mill Hand Advanced Sanitizer
NDC: 71101-054 | Form: GEL
Manufacturer: Veridian Healthcare
Category: otc | Type: HUMAN OTC DRUG LABEL
Date: 20250325

ACTIVE INGREDIENTS: ALCOHOL 70 mL/100 mL
INACTIVE INGREDIENTS: ALOE VERA LEAF; FD&C BLUE NO. 1; GLYCERIN; PROPYLENE GLYCOL; AMINOMETHYLPROPANOL; WATER; .ALPHA.-TOCOPHEROL ACETATE; DENATONIUM BENZOATE; YELLOW 5; ACRYLATES/C10-30 ALKYL ACRYLATE CROSSPOLYMER (60000 MPA.S)

Caring Mill Hand Advanced Sanitizer

Active Ingredient

Ethyl Alcohol 70%

Purpose

Antimicrobial

Uses

Helps reduce bacteria on the skin.

Flammable Keep away from fire or flame

Warnings

For external use only. FLAMMABLE. Keep away from heat or flame

When using this product do not use in or near the eyes. In case of contact rinse eyes thoroughly with water.

Stop use and ask a doctor if irritation or rash appears and last

Keep out of reach of children.

If swallowed, get medical help or contact a Poison Control Center (1-800-222-1222) right away.

Directions

- Put enough product in your palm to cover hands
- Rub hands together briskly until dry.
- Children under 6 years of age should be supervised when using this product.

Other Information

-Store at room temperature

-May discolor certain fabrics or surfaces

Inactive Ingredients

acrylates/C10-30 alkyl acrylate crosspolymer, aloe barbadensis leaf juice, aminomethyl propanol, denatonium benzoate, FD&C blue no. 1, FD&C yellow no. 5, fragrance, glycerin, propylene glycol, tocopheryl acetate, water